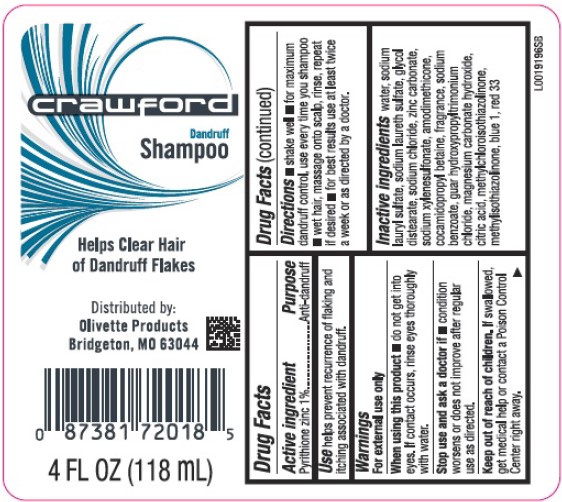 DRUG LABEL: Dandruff
NDC: 90089-153 | Form: SHAMPOO
Manufacturer: TKC Holdings, Inc.
Category: otc | Type: HUMAN OTC DRUG LABEL
Date: 20260217

ACTIVE INGREDIENTS: PYRITHIONE ZINC 1 mg/1 mL
INACTIVE INGREDIENTS: WATER; SODIUM LAURYL SULFATE; SODIUM LAURETH SULFATE; GLYCOL DISTEARATE; SODIUM CHLORIDE; ZINC CARBONATE; SODIUM XYLENESULFONATE; AMODIMETHICONE (800 CST); COCAMIDOPROPYL BETAINE; SODIUM BENZOATE; GUAR HYDROXYPROPYLTRIMONIUM CHLORIDE (1.7 SUBSTITUENTS PER SACCHARIDE); MAGNESIUM CARBONATE HYDROXIDE; CITRIC ACID MONOHYDRATE; METHYLCHLOROISOTHIAZOLINONE; METHYLISOTHIAZOLINONE; FD&C BLUE NO. 1; D&C RED NO. 33

Crawford 153.408/153AZ-BD
Everyday Clean Dandruff Shampoo

Acitive ingredient

Pyrithione zinc 1%

Purpose

Anti-dandruff

Use

helps prevent recurrence of flaking and itching associated with dandruff

Warnings

For external use only

When using this product

- do not get into eyes. If contact occurs, rinse eyes thoroughly with water.

Stop use and ask a doctor if

- condition worsens or does not improve after regular use as directed

Keep out of reach of children.

If swallowed, get medical help or contact a Poison Control Center right away.

Directions

- shake well
- for maximum dandruff control, use every time you shampoo
- wet hair, massage onto scalp, rinse, repeat if desired
- for best results use at least twice a week or as directed by a doctor

inactive ingredients

water, sodium lauryl sulfate, sodium laureth sulfate, glycol distearate, sodium chloride, zinc carbonate, sodium xylenesulfonate, amodimethicone, cocamidopropyl betaine, fragrance, sodium benzoate, guar hydroxypropyltrimonium chloride, magnesium carbonate hydroxide, citric acid, methylchloroisothiazolinone, methylisothiazolinone, blue 1, red 33

Adverse reactions

Distributed by:

Olivette Products

Bridgeton, MO 63044

principal display panel

crawford

Dandruff

Shampoo

Helps Clear Hair of Dandruff Flakes

Distributed by:

Olivette Products

Bridgeton, MO 63044

4 FL OZ (118 mL)